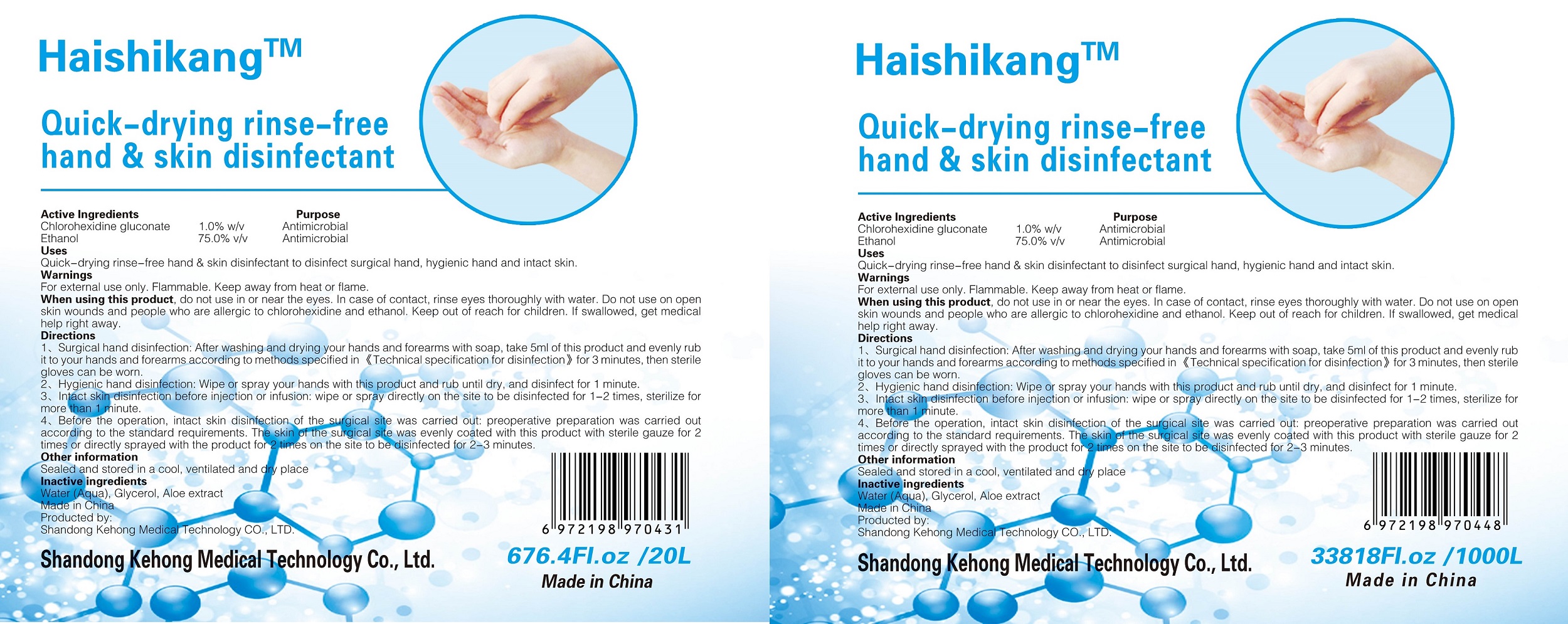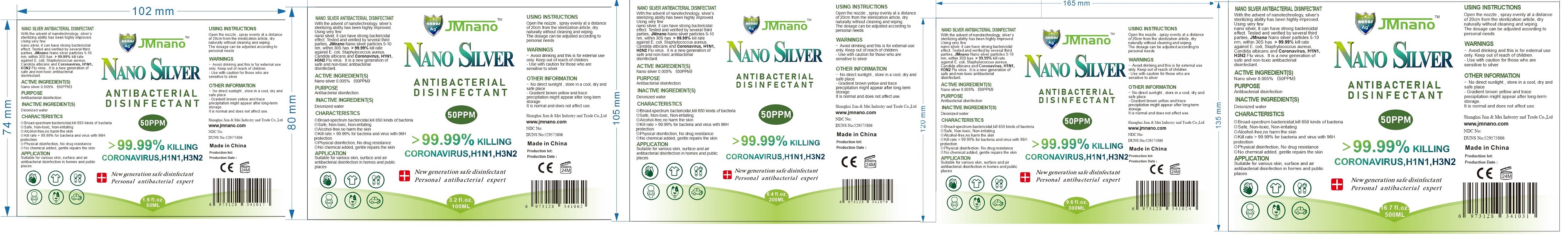 DRUG LABEL: NANO SILVER ANTIBACTERIAL DISINFECTANT
NDC: 76631-015 | Form: LIQUID
Manufacturer: Shanghai Jian & Mei Industry and Trade Co.,Ltd
Category: otc | Type: HUMAN OTC DRUG LABEL
Date: 20200514

ACTIVE INGREDIENTS: SILVER CATION 0.005 g/100 mL
INACTIVE INGREDIENTS: WATER

NANO SILVER ANTIBACTERIAL DISINFECTANT

NANO SILVER ANTIBACTERIAL DISINFECTANT

With the advent of nanotechnology, silver's sterilizing ability has been highly improved Using very few nano silver, it can have strong bactericidal effect. Tested and verified by several third parties, Jmnano Nano silver particles 5-10 nm. within 30 S has >99. 99% kill rateCandida albicans and Coronavirus H1N1,H3N2 Flu virus. It is a new generation of safe and non-toxic antibacterial disinfectant

ACTIVE INGREDIENTS

Nano silver 0.005%(50 PPM)

PURPOSE

Antibacterial disinfection

INACTIVE INGREDIENT(S)

Deionized water

CHARACTERISTICSO

Broad-spectrum bactericidal,kill 650 kinds of bacteria.Safe Non-toxic.Non-irritating.Alcohol-free no harm the skin.Kill rate 99.99% for bacteria and virus with 96 H protection.Physical disinfection,No drug resistance.NO chemical added,gentle repairs the skin

APPLICATION

Suitable for various skin surface and air antibacterial disinfection in homes and public places

USING INSTRUCTIONS

Open the nozzle, spray evenly at a distance of 20 cm from the sterilization article, dry naturally without cleaning The dosage can be adjusted according to personal needs

WARNINGS

- Avoid drinking and this is for external use only. Keep out of reach of children
- Use with caution for those who are sensitive to silver

OTHER INFORMATION

No direct sunlight, store in a cool, dry and safe place
Gradient brown yellow and trace precipitation might appear after long-term storage
It is normal and does not affect use